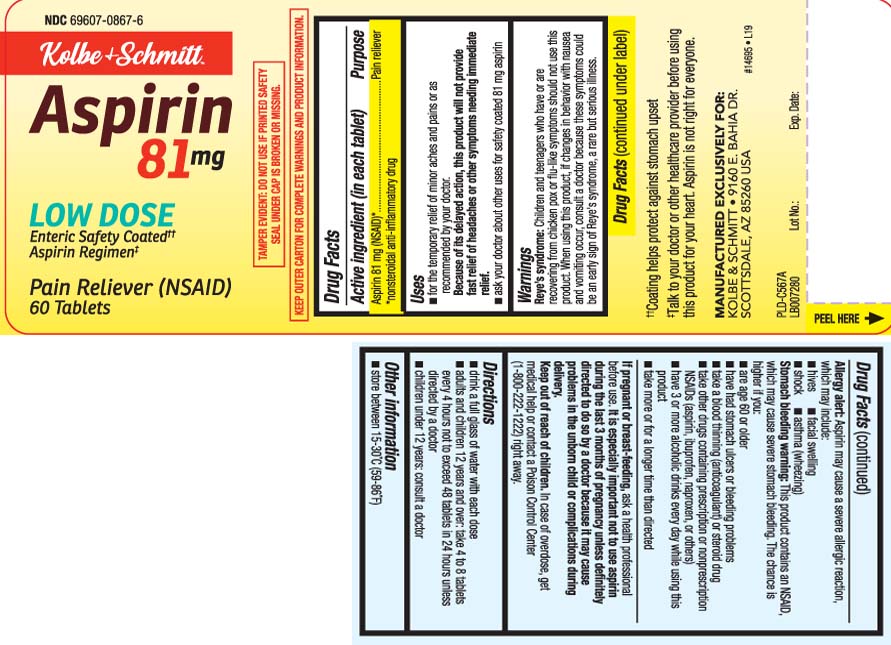 DRUG LABEL: Aspirin
NDC: 69607-0867 | Form: TABLET, COATED
Manufacturer: WR Group, Inc.
Category: otc | Type: HUMAN OTC DRUG LABEL
Date: 20251212

ACTIVE INGREDIENTS: ASPIRIN 81 mg/1 1
INACTIVE INGREDIENTS: D&C YELLOW NO. 10; FD&C YELLOW NO. 6; METHACRYLIC ACID - METHYL METHACRYLATE COPOLYMER (1:1); CELLULOSE, MICROCRYSTALLINE; STARCH, CORN; SILICON DIOXIDE; SODIUM BICARBONATE; SODIUM LAURYL SULFATE; STEARIC ACID; TALC; TITANIUM DIOXIDE; TRIETHYL CITRATE

Drug Facts

Active ingredient (in each tablet)

Aspirin 81 mg (NSAID)*

*nonsteroidal anti-inflammatory drug

Purpose

Pain reliever

Uses

- for the temporary relief of minor aches and pains or as recommended by your doctor. Because of its delayed action, this product will not provide fast relief of headaches or other symptoms needing immediate relief.
- ask your doctor about other uses for safety coated 81 mg aspirin

Warnings

Reye's syndrome: Children and teenagers who have or are recovering from chicken pox or flu-like symptoms should not use this product. When using this product, if changes in behavior with nausea and vomiting occur, consult a doctor because these symptoms could be an early sign of Reye's syndrome, a rare but serious illness.

Allergy alert: Aspirin may cause a severe allergic reaction, which may include:

- hives
- facial swelling
- shock
- asthma (wheezing)

Stomach bleeding warning: This product contains an NSAID, which may cause severe stomach bleeding. The chance is higher if you:

- are age 60 or older
- have had stomach ulcers or bleeding problems
- take a blood thinning (anticoagulant) or steroid drug
- take other drugs containing prescription or nonprescription NSAIDs [aspirin, ibuprofen, naproxen, or others]
- have 3 or more alcoholic drinks every day while using this product
- take more or for a longer time than directed

Do not use

- if you are allergic to aspirin or any other pain reliever/fever reducer.
- if you have ever had an allergic reaction to this product or any of its ingredients

Ask a doctor before use if

- stomach bleeding warning applies to you
- you have a history of stomach problems, such as heartburn
- you have high blood pressure, heart disease, liver cirrhosis, or kidney disease
- you have asthma
- you are taking a diuretic

Ask a doctor or pharmacist before use if you are

taking a prescription drug for

- gout
- diabetes
- arthritis

Stop use and ask a doctor if

- an allergic reaction occurs. Seek medical help right away.
- you experience any of the following signs of stomach bleeding:
  - feel faint
  - vomit blood
  - have bloody or black stools
  - have stomach pain that does not get better
- pain gets worse or lasts more than 10 days
- fever gets worse or last more than 3 days
- redness or swelling is present
- ringing in the ears or loss of hearing occurs
- new symptoms occur

These could be signs of a serious condition

If pregnant or breast-feeding,

ask a health professional before use. It is especially important not to use aspirin during the last 3 months of pregnancy unless definitely directed to do so by a doctor because it may cause problems in the unborn child or complications during delivery.

Keep out of reach of children.

In case of overdose, get medical help or contact a Poison Control Center (1-800-222-1222) right away.

Directions

- drink a full glass of water with each dose
- adults and children 12 years and over: take 4 to 8 tablets every 4 hours not to exceed 48 tablets in 24 hours unless directed by a doctor
- children under 12 years: do not use

Other information

- store between 15-30ºC (59-86ºF)

Inactive ingredients

D&C yellow #10, FD&C yellow #6, methacrylic acid copolymer, microcrystalline cellulose, pregelatinized starch (corn), silicon dioxide, sodium bicarbonate, sodium lauryl sulfate, stearic acid, talc, titanium dioxide, triethyl citrate

Principal Display Panel

Compare to the active ingredient in Bayer® Low Dose Aspirin®†

Aspirin

LOW DOSE

Enteric Safety Coated††

Pain reliever (NSAID)

Tablets

≠Talk to your doctor or other healthcare provider before using this product for your heart.

†This product is not manufactured or distributed by Bayer HealthCare LLC, distributor of Bayer® Low Dose Aspirin.

≠Coating helps protect against stomach upset.

TAMPER EVIDENT: DO NOT USE IF PRINTED SAFETY SEAL UNDER CAP IS BROKEN OR MISSING.

KEEP OUTER CARTON FOR COMPLETE WARNINGS AND PRODUCT INFORMATION.

MANUFACTURED EXCLUSIVELY FOR:

KOLBE & SCHMITT

9160 E. BAHIA DR.

SCOTTSDALE, AZ 85260 USA

Product Label

KOLBE & SCHMITT Low Dose Aspirin